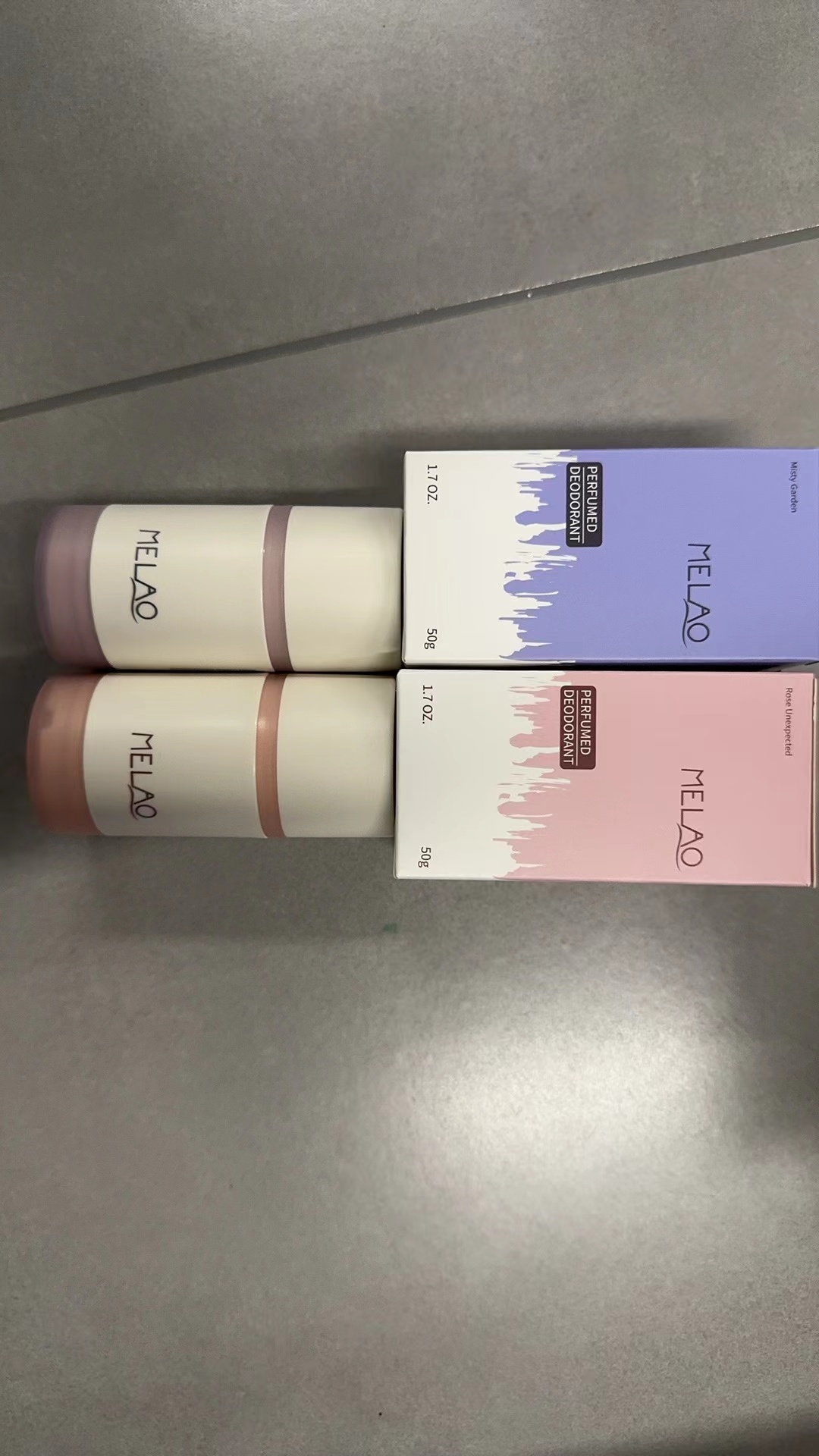 DRUG LABEL: MELAO Perfumed Deodorant
NDC: 83566-579 | Form: STICK
Manufacturer: Guangzhou Yilong Cosmetics Co., Ltd
Category: otc | Type: HUMAN OTC DRUG LABEL
Date: 20240810

ACTIVE INGREDIENTS: PHENOXYETHANOL 2 g/100 g; CALCIUM HYDROXIDE 4 g/100 g
INACTIVE INGREDIENTS: STEARIC ACID 7.3 g/100 g; ETIDRONATE TETRASODIUM 2.3 g/100 g; ETHYLHEXYLGLYCERIN 1 g/100 g; SAURURUS CHINENSIS WHOLE 0.07 g/100 g; WATER 55 g/100 g; MPEG-400-GLY-NEU-GALNAC-THR 9 g/100 g; PARFUMIDINE 0.9 g/100 g; PROPYLENE GLYCOL DIETHYLHEXANOATE 6 g/100 g; GLYCERIN 5 g/100 g; SUCROSE 2.4 g/100 g

MELAO Perfumed Deodorant

Active ingredients

Sodium Hydroxide 4%

Phenoxyethanol 2%

-Inactive ingredients

Water 55%

PEG-400 9%

Propylene Glycol 6%

Glycerin 5%

Stearic Acid 5%

Polysorbate 20 3.7%

Polysorbate 60 3.6%

Sucrose 2.4%

Tetrasodium EDTA 2.3

Ethylhexylglycerin 1%

Parfum 0.9%

Saururus Chinensis Leaf/Root Extract 0.07%

TaraxacumOfficinale (Dandelion) Leaf Extract 0.03%

Purpose

Deodorization

uses

STEP1: Clean and thoroughly dry your skin.

STEP2: Twist the bottom of the product.

STEP3: Gently apply to the underarms or other desired areas.

Warning

.For external use only.

Stop use and ask a doctor if

rash occurs.

Do not use

on damaged or broken skin.

When using this product

keep out of eyes. Rinse withwater to remove.

Keep out of reach of children.

If swallowed, get medical help or contact a Poison Control Center right away.

DOSAGE & ADMINISTRATION

Squeeze out an appropriate amount of sunscreen and spread evenly on skin.